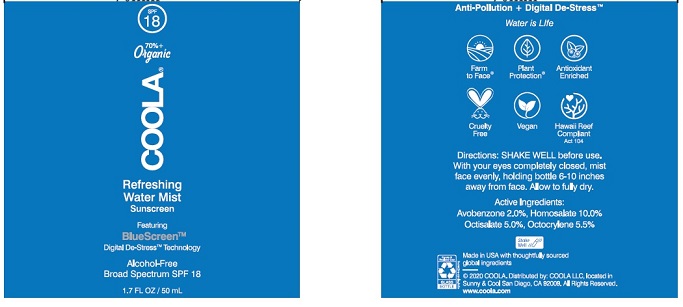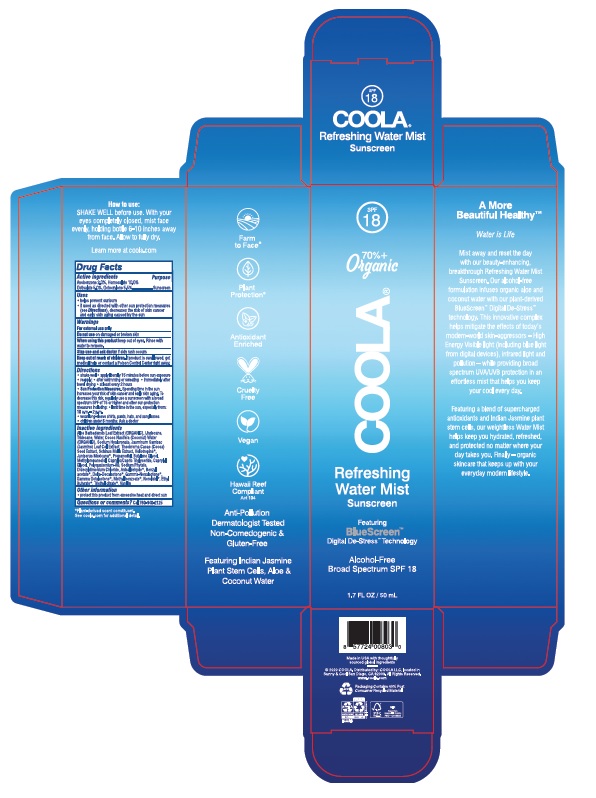 DRUG LABEL: COOLA Refreshing Water Mist SPF 18
NDC: 54111-148 | Form: SPRAY
Manufacturer: Bentley Laboratories, LLC
Category: otc | Type: HUMAN OTC DRUG LABEL
Date: 20231219

ACTIVE INGREDIENTS: AVOBENZONE 2.0 g/100 mL; HOMOSALATE 10.0 g/100 mL; OCTISALATE 5.0 g/100 mL; OCTOCRYLENE 5.5 g/100 mL
INACTIVE INGREDIENTS: ALOE VERA LEAF; UNDECANE; TRIDECANE; WATER; COCONUT WATER; HYALURONATE SODIUM; JASMINUM OFFICINALE LEAF; COCOA; SCHINUS MOLLE FRUITING TOP; PIPERONAL; JUNIPERUS DEPPEANA WOOD OIL; PROPANEDIOL; BUTYLENE GLYCOL; METHYLPROPANEDIOL; MEDIUM-CHAIN TRIGLYCERIDES; CAPRYLYL GLYCOL; POLYQUATERNIUM-80; PHYTATE SODIUM; DIDECYLDIMONIUM CHLORIDE; P-ANISALDEHYDE; BENZYL ACETATE; .DELTA.-DECALACTONE; .GAMMA.-NONALACTONE; .GAMMA.-OCTALACTONE; METHYL BENZOATE; NEROLIDOL; ETHYL BUTYRATE; TRIETHYL CITRATE; VANILLIN

COOLA Refreshing Water Mist Sunscreen Broad Spectrum SPF 18

Drug Facts

Active Ingredients

Avobenzone 2.0%. Homosalate 10.0%

Octisalate 5.0%, Octocrylene 5.5%

Purpose

Sunscreen

Uses

• helps prevent sunburn

• if used as directed with other sun protection measures

(see Directions), decreases the risk of skin cancer

and early skin aging caused by the sun

Warnings

For external use only

Do not use on damaged or broken skin

When using this product keep out of eyes. Rinse with

water to remove.

Stop use and ask doctor if skin rash occurs

Keep out of reach of children. If product is swallowed, get

medical help or contact a Poison Control Center right away.

Directions
• shake well • apply liberally 15 minutes before sun exposure
• reapply: •after swimming or sweating • immediately
after towel drying • at least every 2 hours
• Sun Protection Measures. Spending time in the sun
increases your risk of skin cancer and early aging. To
decrease this risk, regularly use a sunscreen with a broad
spectrum SPF of 15 or higher and other sun protection
measures including: • limit time in the sun, especially from:
10 a.m. - 2 p.m.
• wear long-sleeved shirts, pants, hats, and sunglasses
• children under 6 months: Ask a doctor

Inactive Ingredients
Aloe Barbadensis Leaf Extract (ORGANIC), Undecane,
Tridecane, Water, Cocos Nucifera (Coconut) Water
(ORGANIC), Sodium Hyaluronate, Jasminum Sambac
(Jasmine) Leaf Cell Extract, Theobroma Cacao (Cocoa)
Seed Extract, Schinus Molle Extract, Heliotropine*,
Juniperus Mexicana*, Propanediol, Butylene Glycol,
Methlypropanediol, Caprylic/Capric Triglyceride, Caprylyl
Glycol, Polyquaternium-80, Sodium Phytate,
Didecyldimonium Chloride, Anisaldehyde*, Benzyl
acetate*, Delta-Decalactone*, Gamma-Nonalactone*,
Gamma Octalactone*, Methyl benzoate*, Nerolidol*, Ethyl
Butyrate*, Triethyl citrate*, Vanillin

* Plant-derived scent constituent.

Other information

• protect this product from excessive heat and direct sun

Questions or comments? Call 760-940-2125

COOLA Label

COOLA®

Refreshing Water Mist

Sunscreen

SPF 18

Alcohol-Free

Broad Spectrum SPF 18

1.7 FL OZ / 50 mL

Distributed by: COOLA LLC, located in

Sunny & Cool San Diego, CA 92009

www.coola.com

res